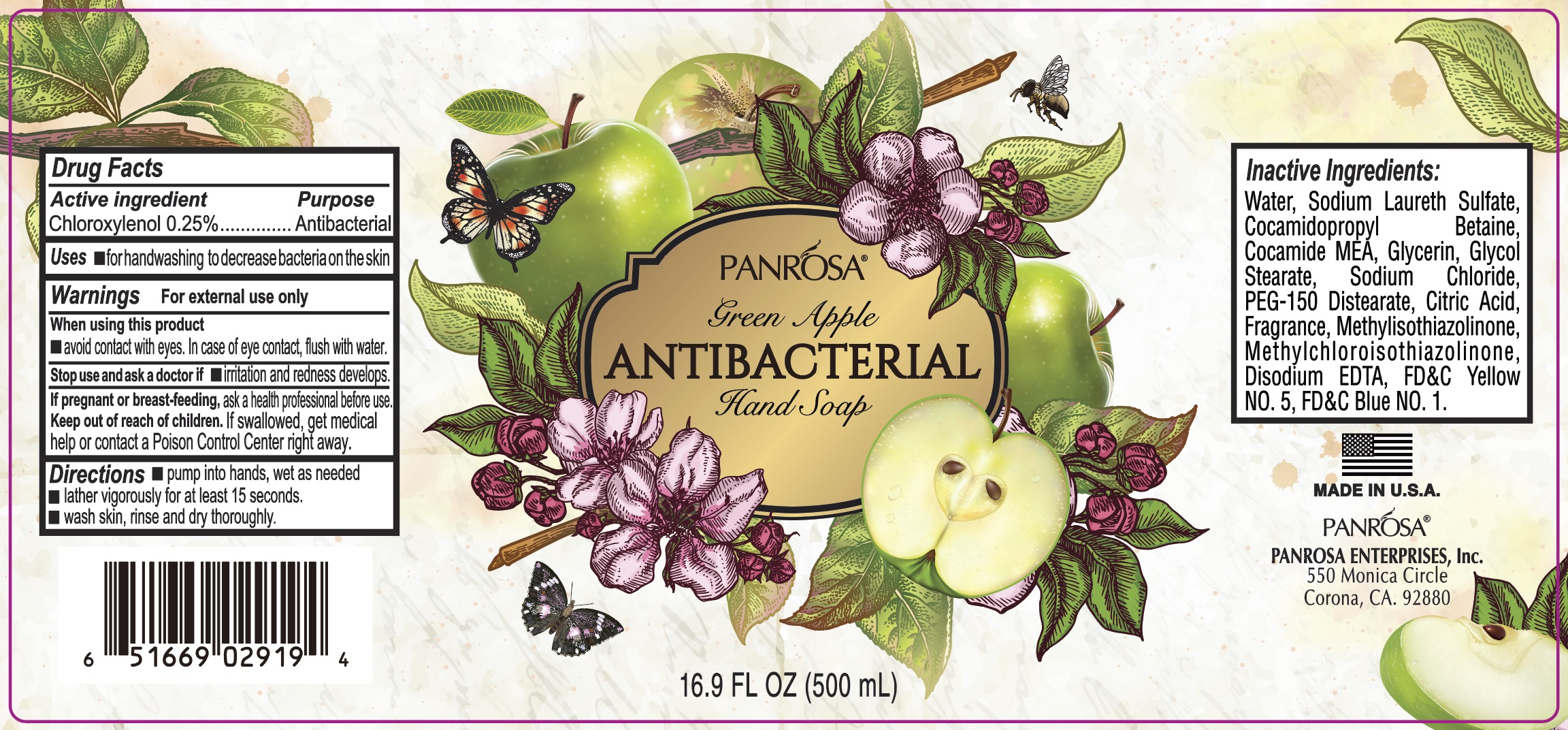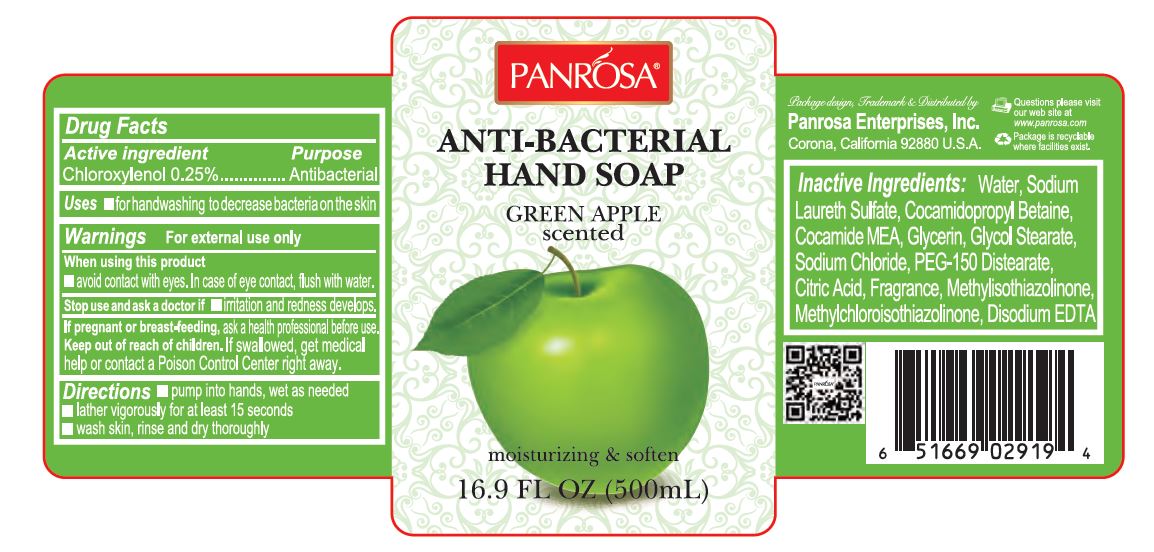 DRUG LABEL: Antibacterial Hand Green Apple Scented
NDC: 50302-500 | Form: LIQUID
Manufacturer: PANROSA ENTERPRISES, INC.
Category: otc | Type: HUMAN OTC DRUG LABEL
Date: 20211021

ACTIVE INGREDIENTS: CHLOROXYLENOL 2.5 mg/1 mL
INACTIVE INGREDIENTS: WATER; SODIUM LAURETH SULFATE; COCAMIDOPROPYL BETAINE; COCO MONOETHANOLAMIDE; GLYCERIN; GLYCOL STEARATE; SODIUM CHLORIDE; PEG-150 DISTEARATE; CITRIC ACID MONOHYDRATE; METHYLISOTHIAZOLINONE; METHYLCHLOROISOTHIAZOLINONE; EDETATE DISODIUM

Antibacterial Hand Soap Green Apple Scented

Active ingredient

Chloroxylenol 0.25%

Purpose

Antibacterial

Uses

- for handwashing to decrease bacteria on the skin

Warnings

For external use only

When using this product

- Avoid contact with eyes. In case of eye contact, flush with water.

Stop use and ask a doctor if

- irritation and redness develops.

If pregnant or breast-feeding,

ask a health professional before use.

Keep out of reach of children.

If swallowed, get medical help or contact a Poison Control Center right away.

Directions

- pump into hands, wet as needed
- lather vigorously for at leat 15 seconds
- wash skin, rinse and dry thoroughly

Inactive Ingredients:

Water, Sodium Laureth Sulfate, Cocamidopropyl Betaine, Cocamide MEA, Glycerin, Glycol Stearate, Sodium Chloride, Peg-150 Distearate, Citric Acid, Fragrance, Methylisothiazolinone Methylchloroisothiazolinone, Disodium EDTA